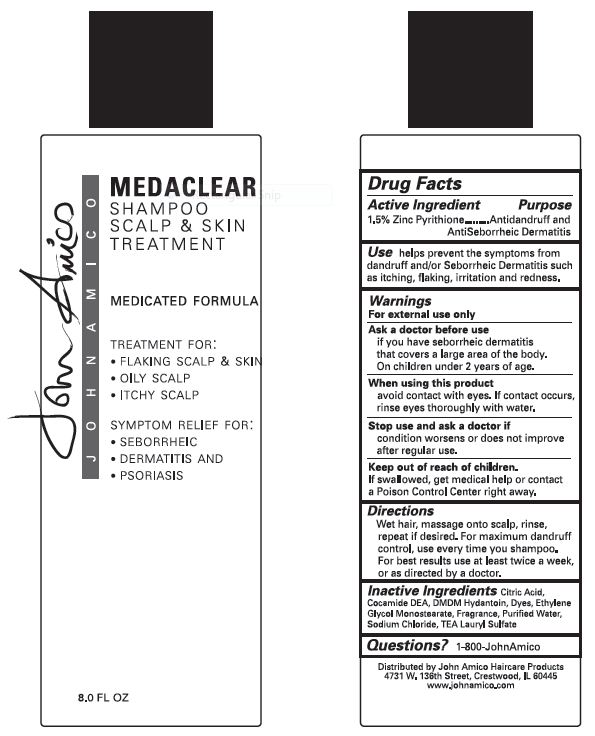 DRUG LABEL: Medaclear
NDC: 51290-011 | Form: SHAMPOO
Manufacturer: Amico Educational Concepts, Inc.
Category: otc | Type: HUMAN OTC DRUG LABEL
Date: 20111229

ACTIVE INGREDIENTS: PYRITHIONE ZINC 15.0 g/1.0 L
INACTIVE INGREDIENTS: WATER; CITRIC ACID MONOHYDRATE; COCO DIETHANOLAMIDE; DMDM HYDANTOIN; GLYCOL STEARATE; SODIUM CHLORIDE; TROLAMINE LAURYL SULFATE

Medaclear Shampoo

Active ingredient

Zinc Pyrithione 1.5%

Purpose

Antidandruff and Antisebborrheic Dermatitis

Use

helps prevent the symptoms from dandruff and/or Seborrheic Dermatitus such as itching, flaking, irritation and redness.

Warnings

Ask a doctor before use

if you have seborrheic dermatitis that covers a large area of the body.

On children under 2 years of age.

When using this product

avoid contact with eyes. If contact occurs, rinse eyes thoroughly with water.

Stop use and ask a doctor if

condition worsens or does not improve after regular use.

Keep out of reach of children

If swallowed, get medical help or contact a Poison Control Center right away.

Directions

Wet hair, massage into scalp, rinse, repeat if desired. For maximum dandruff control, use every time you shampoo. For best results, use twice a week, or as directed by a doctor.

Other information

Shampoo Scalp & Skin Treatment

Medicated Formula

Treatment for:

- Flaking Scalp & Skin
- Oily Scalp
- Itchy Scalp

Symptom Relief for:

- Seborrheic Dermatitus and Psoriasis

Inactive ingredients

Citric Acid, Cocamide DEA, DMDM Hydantoin, Dyes, Ethylene Glycol Monostearate, Fragrance, Purified Water, Sodium Chloride, TEA Lauryl Sulfate

Questions?

1-800-JohnAmico

Principal Display Panel

8oz label:

8oz Label

Distributed By

John Amico Haircare Products

4731 W. 136th Street, Crestwood, IL 60445

www.johnamico.com